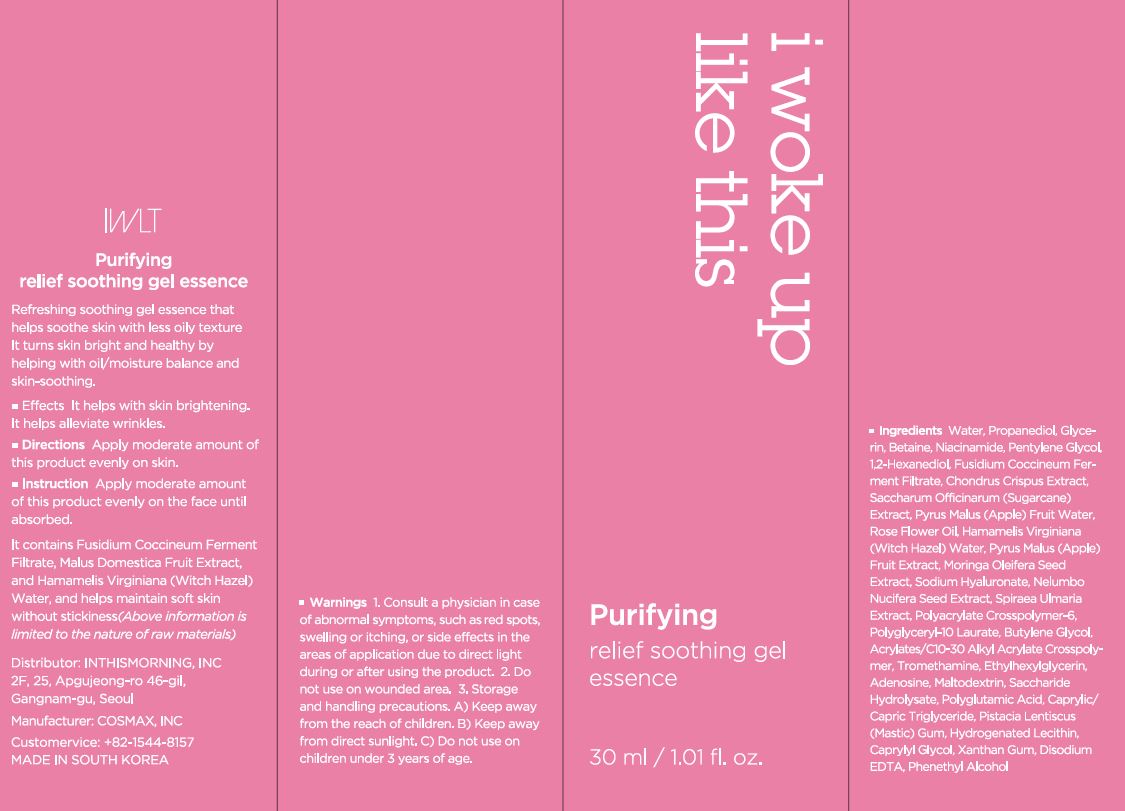 DRUG LABEL: Purifying relief soothing gel essence
NDC: 71217-0054 | Form: LIQUID
Manufacturer: inthismorning co ltd
Category: otc | Type: HUMAN OTC DRUG LABEL
Date: 20230130

ACTIVE INGREDIENTS: .BETA.-CITRONELLOL, (R)- 0.0090408 g/100 mL
INACTIVE INGREDIENTS: GLYCERIN; COCONUT WATER

Drug Facts

ACTIVE INGREDIENT

citronellol

INACTIVE INGREDIENT

Water
Propanediol
Glycerin
Betaine
Niacinamide
Pentylene Glycol
1,2-Hexanediol
Fusidium Coccineum Ferment Filtrate
Polyacrylate Crosspolymer-6
Chondrus Crispus Extract
Polyglyceryl-10 Laurate
Butylene Glycol
Saccharum Officinarum (Sugarcane) Extract
Acrylates/C10-30 Alkyl Acrylate Crosspolymer
Tromethamine
Pyrus Malus (Apple) Fruit Water
Xanthan Gum
Ethylhexylglycerin
Adenosine
Disodium EDTA
Rose Flower Oil
Hamamelis Virginiana (Witch Hazel) Water
Pyrus Malus (Apple) Fruit Extract
Maltodextrin
Moringa Oleifera Seed Extract
Saccharide Hydrolysate
Polyglutamic Acid
Sodium Hyaluronate
Caprylic/Capric Triglyceride
Pistacia Lentiscus (Mastic) Gum
Hydrogenated Lecithin
Nelumbo Nucifera Seed Extract
Spiraea Ulmaria Extract
Phenethyl Alcohol
Caprylyl Glycol

PURPOSE

skin brightening, alleviate wrinkles

keep out or reach of the children

INDICATIONS AND USAGE

apply moderate amount of this product evenly on the face until absorbed

WARNINGS

This product is for exeternal use only. Do not use for internal use
Storage and handling precautions
If possible, avoid direct sunlight and store in cool and area of low humidity in order to maintain the quality of the product and avoid misuse
Avoid placing the product near fire and store out in reach of children

- consult a physician in case of abnormal symptoms, such as red spots, swelling or itching, or side effects in the areas of application due to direct light during or after using the product

- do not use on wounded area

DOSAGE AND ADMINISTRATION

for external use only